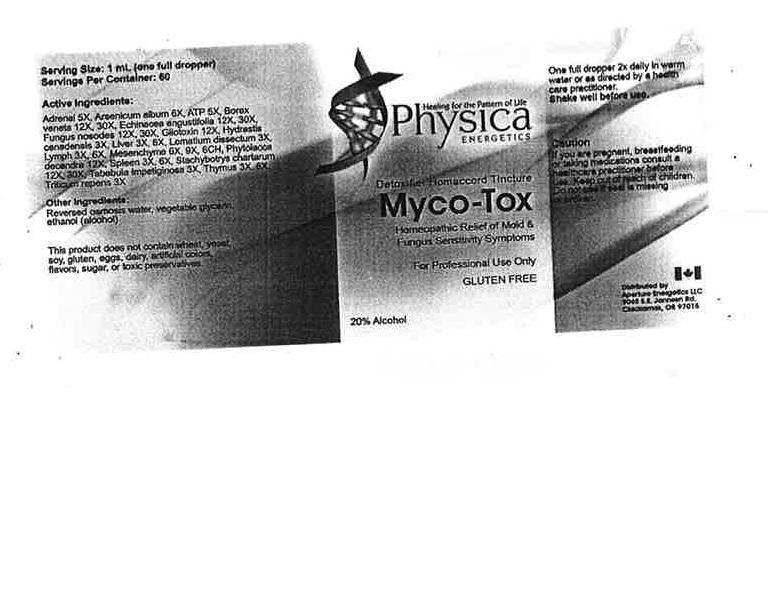 DRUG LABEL: Myco-Tox
NDC: 54118-7103 | Form: SOLUTION/ DROPS
Manufacturer: ABCO Labratories, Inc.
Category: homeopathic | Type: HUMAN OTC DRUG LABEL
Date: 20150813

ACTIVE INGREDIENTS: BOS TAURUS ADRENAL GLAND 5 [hp_X]/60 mL; ARSENIC 6 [hp_X]/60 mL; ADENOSINE TRIPHOSPHATE 5 [hp_X]/60 mL; SODIUM BORATE 12 [hp_X]/60 mL; ECHINACEA ANGUSTIFOLIA 12 [hp_X]/60 mL; GLIOTOXIN 12 [hp_X]/60 mL; HYDRASTIS CANADENSIS WHOLE 3 [hp_X]/60 mL; BEEF LIVER 3 [hp_X]/60 mL; LOMATIUM DISSECTUM WHOLE 3 [hp_X]/60 mL; BOS TAURUS LYMPH 3 [hp_X]/60 mL; BOS TAURUS MESENCHYME 6 [hp_X]/60 mL; PHYTOLACCA AMERICANA WHOLE 12 [hp_X]/60 mL; BOS TAURUS SPLEEN 3 [hp_X]/60 mL; STACHYBOTRYS CHARTARUM 12 [hp_X]/60 mL; TABEBUIA IMPETIGINOSA WHOLE 3 [hp_X]/60 mL; BOS TAURUS THYMUS 3 [hp_X]/60 mL; ELYMUS REPENS WHOLE 3 [hp_X]/60 mL
INACTIVE INGREDIENTS: ALCOHOL; GLYCERIN; WATER

Myco-Tox

WARNINGS

If you are pregnant, breasfeeding or taking medications consult a health care practitioner before use.

Keep out of reach of children.

Do not use if seal is missing or broken.

Keep out of reach of children.

INDICATIONS AND USAGE

Detoxifier Homaccord Tincture.

For Professional Use Only.

Gluten Free.

PURPOSE

Homeopathic Relief of Mold & Fngus Sensitivity Symptoms.

DOSAGE AND ADMINISTRATION

One full dropper 2x daily in warm water or as directed by a health care practitioner.

Shake well before use.

INACTIVE INGREDIENT

Reversed osmosis water, vegetable glycerin, alcohol (ethanol).

ACTIVE INGREDIENT

Adrenal 5x, Arsenicum Album 6x, ATP 5x, Borax Veneta 12x, 30x, Echinacea Angustifolia 12x, 30x, Gliotoxin12x, Hydrastis Canadensis 3x, Liver 3x, 6x, Lomatium Dissectum 3x, Lymph 3x, 6x, Mesenchyme 6x, 9x, 6c, Phytolacca 12x, Spleen 3x, 6x, Stachybotrys Chartarum 12x, 30x, Tabebuia Imptetiginosa 3x, Thymus 3x, 6x, Triticum Repens 3x.